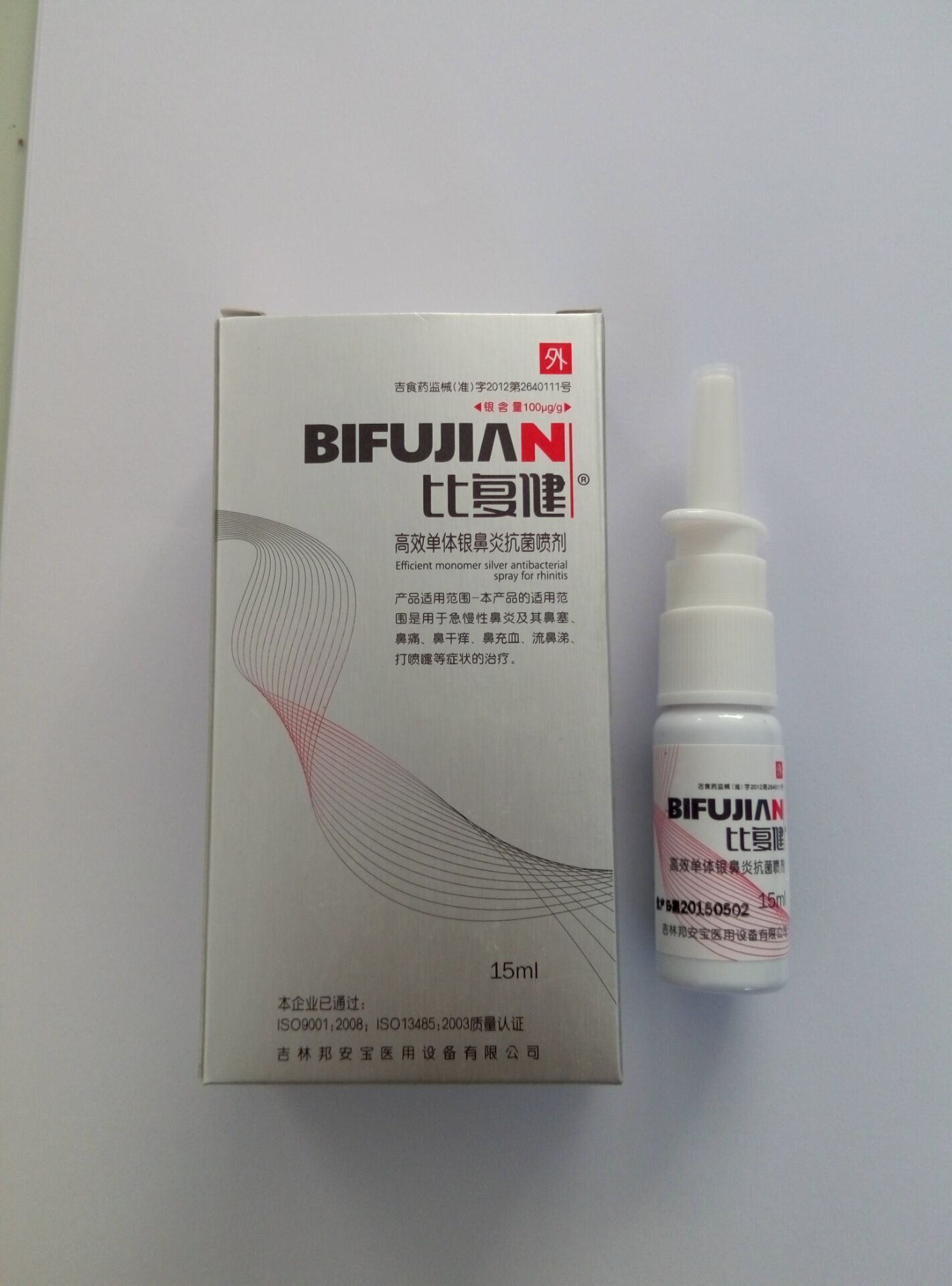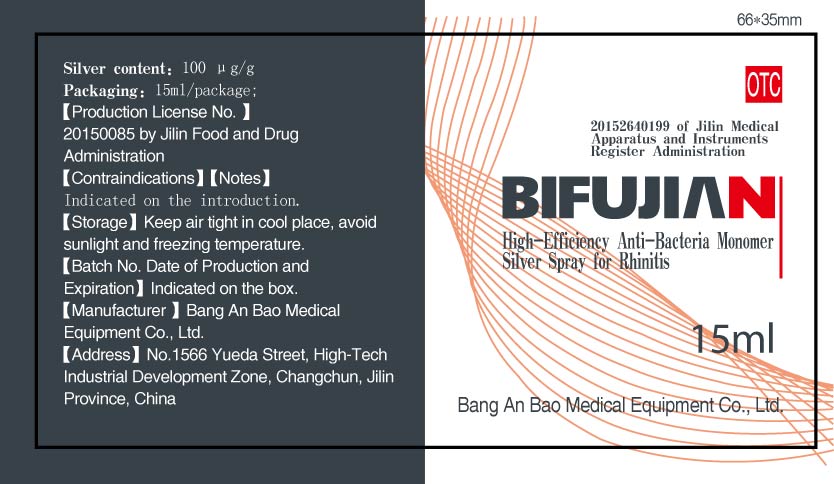 DRUG LABEL: Bi Fu Jian High-Efficiency Anti-Bacteria Monomer Silver Sprays for Rhinitis
NDC: 60659-0303 | Form: LIQUID
Manufacturer: Bang An Bao Medical Equipment Co., Ltd.
Category: homeopathic | Type: HUMAN OTC DRUG LABEL
Date: 20160108

ACTIVE INGREDIENTS: SILVER 1500 ug/15 mL
INACTIVE INGREDIENTS: SODIUM CHLORIDE 20000 ug/15 mL; WATER 14978500 ug/15 mL

Active ingredient

Silver content: 100 μg/mL, 1500 μg/15mL

Purpose

Acute rhinitis; chronic rhinitis; rhinobyon, rhinalgia, dry and itchy nose, nasal congestion, rhinorrhea, sneeze.

Indcations and usage

Acute rhinitis; chronic rhinitis; rhinobyon, rhinalgia, dry and itchy nose, nasal congestion, rhinorrhea, sneeze.

Topical use: Spraying into the nasal cavity.

Dosage

4 sprays each time and 3 times each day, for 7 consecutive days, or longer if serious.

4 times each day for chronic rhinitis patient, for 7 consecutive days, or longer if serious.

Warnings

Contraindications:
1, Not for virgins.
2, Do not use if allergic to silver.
3, Pregnant women shall follow doctor advice.
Notes:
1, Do not use if package is broken; do not use with medicine that contains Vaseline, chlorine, iodine or hydrogen peroxide.
2, This product is for external use only; do not take in.
3, Keep away from clothes to prevent contamination.

Out of children

Keep out of reach of children. If the product is swallowed, get medical help or contact a Poison Control Center right away.

Inactive ingredient

Sodium chloride: 20000 μg/15mL

Water: 14978500 μg/15mL

Label

Package label

Carton label